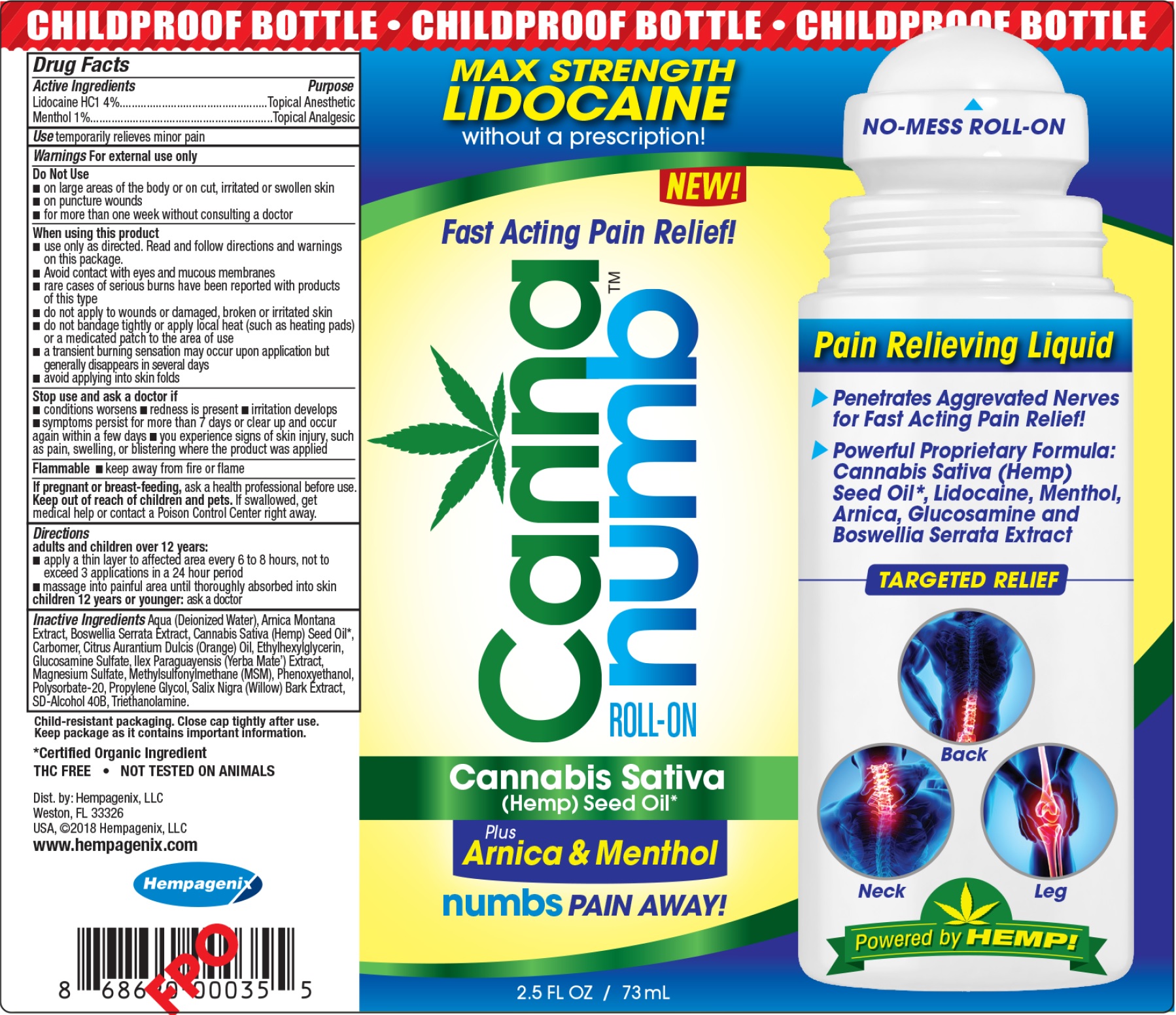 DRUG LABEL: CANNA NUMB Roll On
NDC: 72614-265 | Form: LIQUID
Manufacturer: Cannanumb LLC
Category: otc | Type: HUMAN OTC DRUG LABEL
Date: 20250217

ACTIVE INGREDIENTS: LIDOCAINE HYDROCHLORIDE 40 mg/1 mL; MENTHOL 10 mg/1 mL
INACTIVE INGREDIENTS: WATER; ARNICA MONTANA; CANNABIS SATIVA SEED OIL; CARBOXYPOLYMETHYLENE; ORANGE OIL; ETHYLHEXYLGLYCERIN; GLUCOSAMINE SULFATE; ILEX PARAGUARIENSIS LEAF; MAGNESIUM SULFATE, UNSPECIFIED FORM; DIMETHYL SULFONE; PHENOXYETHANOL; POLYSORBATE 20; PROPYLENE GLYCOL; TROLAMINE

CANNA NUMB Roll-On

Active Ingredients

Lidocaine HCl 4%

Menthol 1%

Purpose

Topical Anesthetic

Topical Analgesic

Uses:

- temporarily relieves minor pain

Warnings:

For external use only.

Do not use

- on large areas of the body or on cut, irritated or swollen skin
- on puncture wounds
- for more than one week without consulting a doctor

When using this product

- use only as directed. Read and follow directions and warnings on this package.
- Avoid contact with eyes and mucous membranes
- rare cases of serious burns have been reported with products of this type
- do not apply to wounds or damaged, broken or irritated skin
- do not bandage tightly or apply local heat (such as heating pads) or a medicated patch to the area of use
- a transient burning sensation may occur upon application but generally disappears in several days
- avoid applying into skin folds

Stop use and ask a doctor if

- conditions worsens
- redeness is present
- irritation develops
- symptoms persist for more than 7 days or clear up and occur again within a few days
- you experience signs of skin injury, such as pain, swelling, or blistering where the product was applied
- - keep away from fire or flame Flammable

If pregnant or breast-feeding,

ask a health professional before use.

Keep out of reach of children and pets.

If swallowed, get medical help or contact a Poison Control Center right away.

Directions:

adults and children over 12 years:

- apply a thin layer to affected area every 6 to 8 hours, not to exceed 3 applications in a 24 hour period
- massage into painful area until thoroughly absorbed into skin
- ask a doctor children 12 years or younger:

Inactive Ingredients:

Aqua (Deionized Water), Arnica Montana Extract, Boswellia Serrata Extract, Cannabis Sativa (Hemp) Seed Oil, Carbomer, Citrus Aurantium Dulcis (Orange) Oil, Ethylhexylglycerin, Glucosamine Sulfate, Ilex Paraguayensis (Yerba Mate) Extract, Magnesium Sulfate, Methylsulfonylemthane (MSM), Phenoxyethanol, Polysorbate-20, Propylene Glycol, Salix Nigra (Willow) Bark Extract, Sd-Alcohol 40B, Triethanolamine.